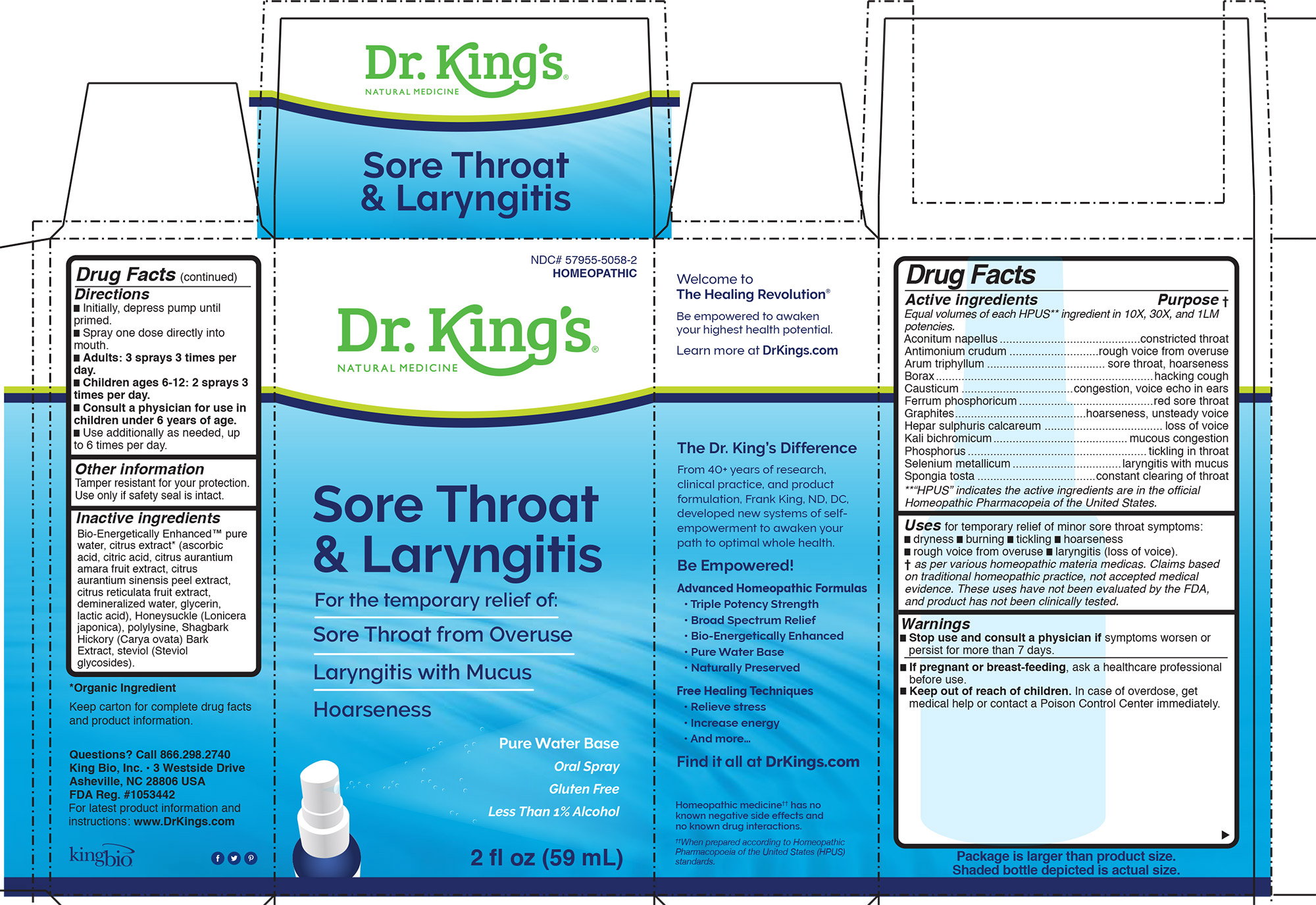 DRUG LABEL: Sore Throat and Laryngitis
NDC: 57955-5058 | Form: LIQUID
Manufacturer: King Bio Inc.
Category: homeopathic | Type: HUMAN OTC DRUG LABEL
Date: 20200709

ACTIVE INGREDIENTS: ACONITUM NAPELLUS 10 [hp_X]/59 mL; ANTIMONY TRISULFIDE 10 [hp_X]/59 mL; ARISAEMA TRIPHYLLUM ROOT 10 [hp_X]/59 mL; SODIUM BORATE 10 [hp_X]/59 mL; CAUSTICUM 10 [hp_X]/59 mL; FERROSOFERRIC PHOSPHATE 10 [hp_X]/59 mL; GRAPHITE 10 [hp_X]/59 mL; CALCIUM SULFIDE 10 [hp_X]/59 mL; POTASSIUM DICHROMATE 10 [hp_X]/59 mL; PHOSPHORUS 10 [hp_X]/59 mL; SELENIUM 10 [hp_X]/59 mL; SPONGIA OFFICINALIS SKELETON, ROASTED 10 [hp_X]/59 mL
INACTIVE INGREDIENTS: WATER; CARYA OVATA BARK; LONICERA JAPONICA FLOWER; POLY-L-LYSINE (30000-70000 MW); REBAUDIOSIDE A

Sore Throat and Laryngitis

HPUS active ingredients

Equal volumes of each ingredient in 10X, 30X, and 1LM potencies.

Aconitum napellus, Antimonium crudum, Arum triphyllum, Borax, Causticum, Ferrum phosphoricum, Graphites, Hepar sulphuris calcareum, Kali bichromicum, Phosphorus, Selenium metallicum, Spongia tosta

INDICATIONS AND USAGE

Uses for temporary relief of minor sore throat symptoms:

- dryness
- burning
- tickling
- hoarseness
- rough voice from overuse
- laryngitis (loss of voice).

† as per various homeopathic materia medicas. Claims based
on traditional homeopathic practice, not accepted medical
evidence. These uses have not been evaluated by the FDA,
and product has not been clinically tested.

Warnings

Stop use and consult a physician if symptoms worsen or
persist for more than 7 days.

PREGNANCY OR BREAST FEEDING

If pregnant or breast-feeding, ask a healthcare professional
before use.

Keep out of reach of children. In case of overdose, get
medical help or contact a Poison Control Center immediately.

Directions:

- Initially, depress pump until primed.
- Spray one dose directly into mouth.
- Adults: 3 sprays 3 times per day.
- Children ages 6-12: 2 sprays 3 times per day.
- Consult a physician for use in children under 6 years of age.
- Use additionally as needed, up to 6 times per day.

Other Information:

Tamper resistant for your protection. Use only if safety seal is intact.

Inactive Ingredients:

Bio-Energetically Enhanced™ pure
water, citrus extract* (ascorbic
acid, citric acid, citrus aurantium
amara fruit extract, citrus
aurantium sinensis peel extract,
citrus reticulata fruit extract,
demineralized water, glycerin,
lactic acid), Honeysuckle (Lonicera
japonica), polylysine, Shagbark
Hickory (Carya ovata) Bark
Extract, steviol (Steviol
glycosides).

HPUS active ingredients Purpose

Equal volumes of each HPUS** ingredient in 10X, 30X, and 1LM
potencies.
Aconitum napellus............................................constricted throat
Antimonium crudum ............................rough voice from overuse
Arum triphyllum ..................................... sore throat, hoarseness
Borax....................................................................hacking cough
Causticum ...................................congestion, voice echo in ears
Ferrum phosphoricum..........................................red sore throat
Graphites.........................................hoarseness, unsteady voice
Hepar sulphuris calcareum ..................................... loss of voice
Kali bichromicum..........................................mucous congestion
Phosphorus........................................................tickling in throat
Selenium metallicum..................................laryngitis with mucus
Spongia tosta .....................................constant clearing of throat
**“HPUS” indicates the active ingredients are in the official
Homeopathic Pharmacopeia of the United States.

Questions? Call 866.298.2740
King Bio, Inc. • 3 Westside Drive
Asheville, NC 28806 USA
FDA Reg. #1053442

For latest product information and
instructions: www.DrKings.com